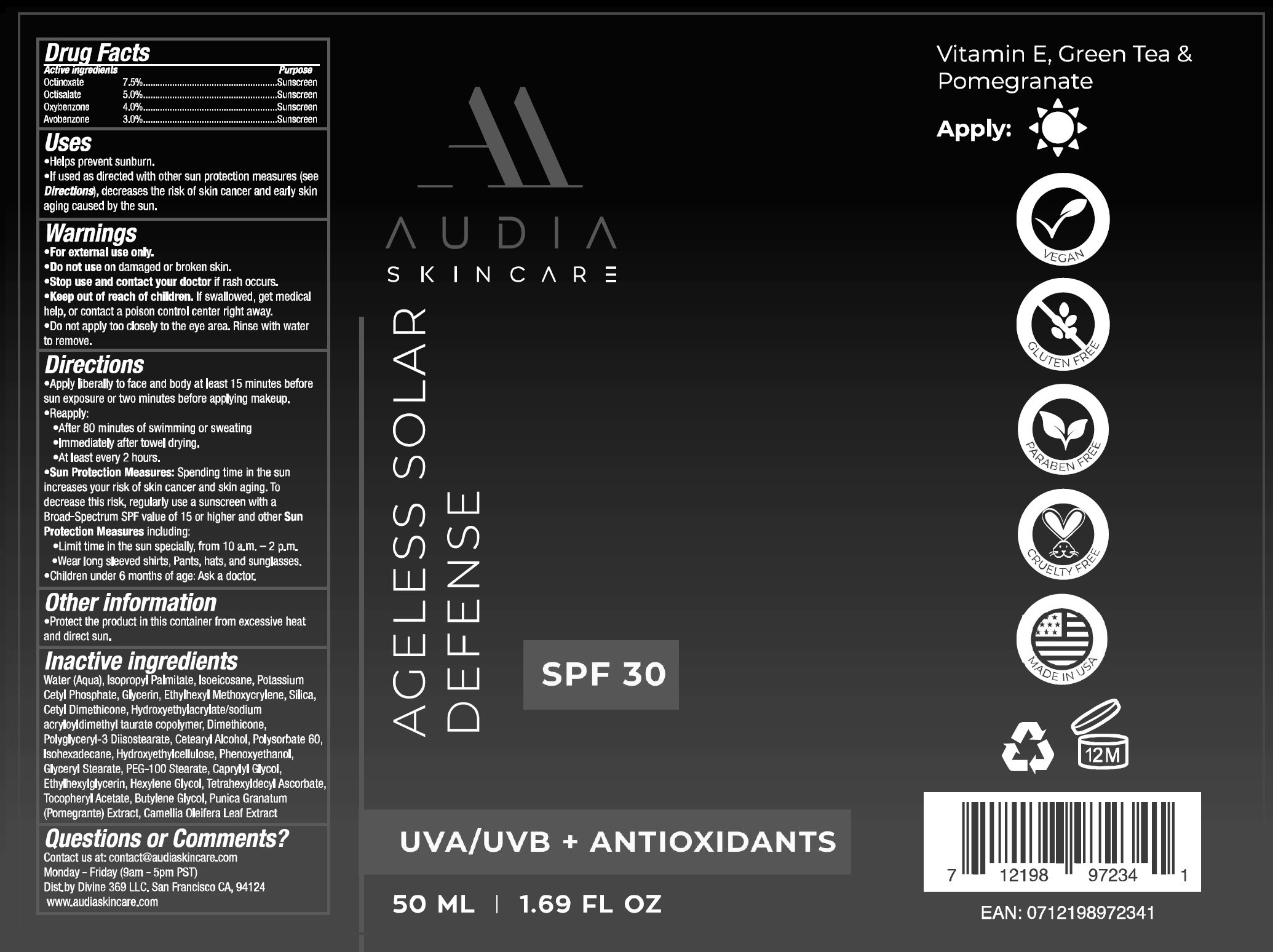 DRUG LABEL: AGELESS SOLAR DEFENSE (SPF 30)
NDC: 82084-0011 | Form: CREAM
Manufacturer: Divine 369 LLC
Category: otc | Type: HUMAN OTC DRUG LABEL
Date: 20230131

ACTIVE INGREDIENTS: OCTINOXATE 75 mg/1 mL; OCTISALATE 50 mg/1 mL; OXYBENZONE 40 mg/1 mL; AVOBENZONE 30 mg/1 mL
INACTIVE INGREDIENTS: WATER; ISOPROPYL PALMITATE; ISOEICOSANE; POTASSIUM CETYL PHOSPHATE; GLYCERIN; ETHYLHEXYL METHOXYCRYLENE; SILICON DIOXIDE; CETYL DIMETHICONE 25; DIMETHICONE; POLYGLYCERYL-3 DIISOSTEARATE; CETOSTEARYL ALCOHOL; POLYSORBATE 60; ISOHEXADECANE; HYDROXYETHYL CELLULOSE, UNSPECIFIED; PHENOXYETHANOL; GLYCERYL MONOSTEARATE; PEG-100 STEARATE; CAPRYLYL GLYCOL; ETHYLHEXYLGLYCERIN; HEXYLENE GLYCOL; TETRAHEXYLDECYL ASCORBATE; .ALPHA.-TOCOPHEROL ACETATE; BUTYLENE GLYCOL; POMEGRANATE; CAMELLIA OLEIFERA LEAF

AGELESS SOLAR DEFENSE (SPF 30)

Active ingredients

Octinoxate 7.5%
Octisalate 5.0%
Oxybenzone 4.0%
Avobenzone 3.0%

Purpose

Sunscreen

Uses

- Helps prevent sunburn.
- If used as directed with other sun protection measures (see Directions), decreases the risk of skin cancer and early skin aging caused by the sun.

Warnings

- For external use only.

Do not use

- on damaged or broken skin.

Stop use and contact your doctor if

- rash occurs.

Keep out of reach of children.

- If swallowed, get medical help, or contact a poison control center right away.
- Do not apply too closely to the eye area. Rinse with water to remove.

Directions

- Apply liberally to face and body at least 15 minutes before sun exposure or two minutes before applying makeup.
- Reapply:
- After 80 minutes of swimming or sweating
- Immediately after towel drying.
- At least every 2 hours.
- Sun Protection Measures: Spending time in the sun increases your risk of skin cancer and skin aging. To decrease this risk, regularly use a sunscreen with a Broad-Spectrum SPF value of 15 or higher and other Sun Protection Measures including:
- Limit time in the sun specially, from 10 a.m. - 2 p.m.
- Wear long sleeved shirts, pants, hats and sunglasses.
- Children under 6 months of age: Ask a doctor.

Other information

- Protect the product in this container from excessive heat and direct sun.

Inactive ingredients

Water (Aqua), Isopropyl Palmitate, Isoeicosane, Potassium Cetyl Phosphate, Glycerin, Ethylhexyl Methoxycrylene, Silica, Cetyl Dimethicone, Hydroxyethylacrylate/sodium acryloyldimethyl taurate copolymer, Dimethicone, Polyglyceryl-3 Diisostearate, Cetearyl Alcohol, Polysorbate 60, Isohexadecane, Hydroxyethylcellulose, Phenoxyethanol, Glyceryl Stearate, PEG-100 Stearate, Caprylyl Glycol, Ethylhexylglycerin, Hexylene Glycol, Tetrahexyldecyl Ascorbate, Tocopheryl Acetate, Butylene Glycol, Punica Granatum (Pomegranate) Extarct, Camellia Oleifera Leaf Extract

Questions or Comments?

Contact us at: contact@audiaskincare.com

Monday - Friday (9am - 5pm PST)

Dist-by Divine 369 LLC. San Francisco CA, 94124

www.audiaskincare.com